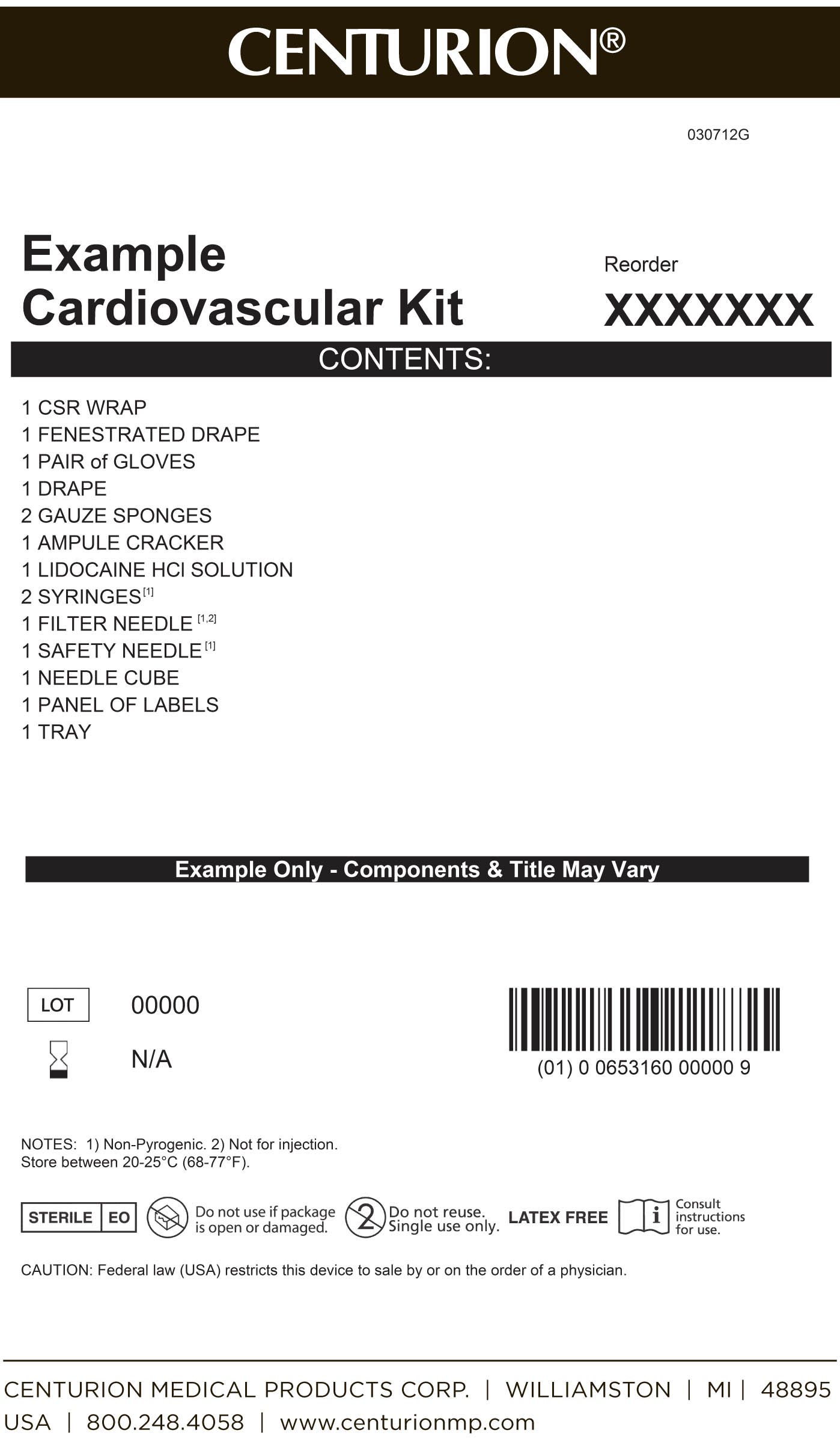 DRUG LABEL: Cardiovascular Procedure Kit
NDC: 24840-1102 | Form: KIT | Route: INFILTRATION
Manufacturer: Centurion Medical Products
Category: other | Type: MEDICAL DEVICE
Date: 20120314

ACTIVE INGREDIENTS: LIDOCAINE HYDROCHLORIDE ANHYDROUS 10 mg/1 mL
INACTIVE INGREDIENTS: Sodium Chloride 7 mg/1 mL; Water; Sodium Hydroxide; Hydrochloric Acid

Cardiovascular ProcedureKit

Drug Description

AQUEOUS SOLUTIONS FOR INFILTRATION

AND NERVE BLOCK

Ampul

Plastic Multiple-dose Fliptop Vial

Glass Teartop Vial

Rx only

DESCRIPTION

Lidocaine Hydrochloride Injection, USP is a sterile, nonpyrogenic solution of lidocaine hydrochloride in water for injection for parenteral administration in various concentrations with characteristics as follows:

Concentration 0.5% 1% 1.5% 2%

mg/mL lidocaine HCl (anhyd.) 5 10 15 20

mg/mL sodium chloride 8 7 6.5 6

Multiple-dose vials contain 0.1% of methylparaben added as preservative. May contain sodium hydroxide and/or hydrochloric acid for pH adjustment. The pH is 6.5 (5.0 to 7.0).

Lidocaine is a local anesthetic of the amide type.

Lidocaine Hydrochloride, USP is chemically designated 2-(diethylamino)-N-(2,6-dimethylphenyl)-acetamide monohydrochloride monohydrate, a white powder freely soluble in water. The molecular weight is 288.82.

Cardiovascular Procedure Kit - Primary Label

MM1